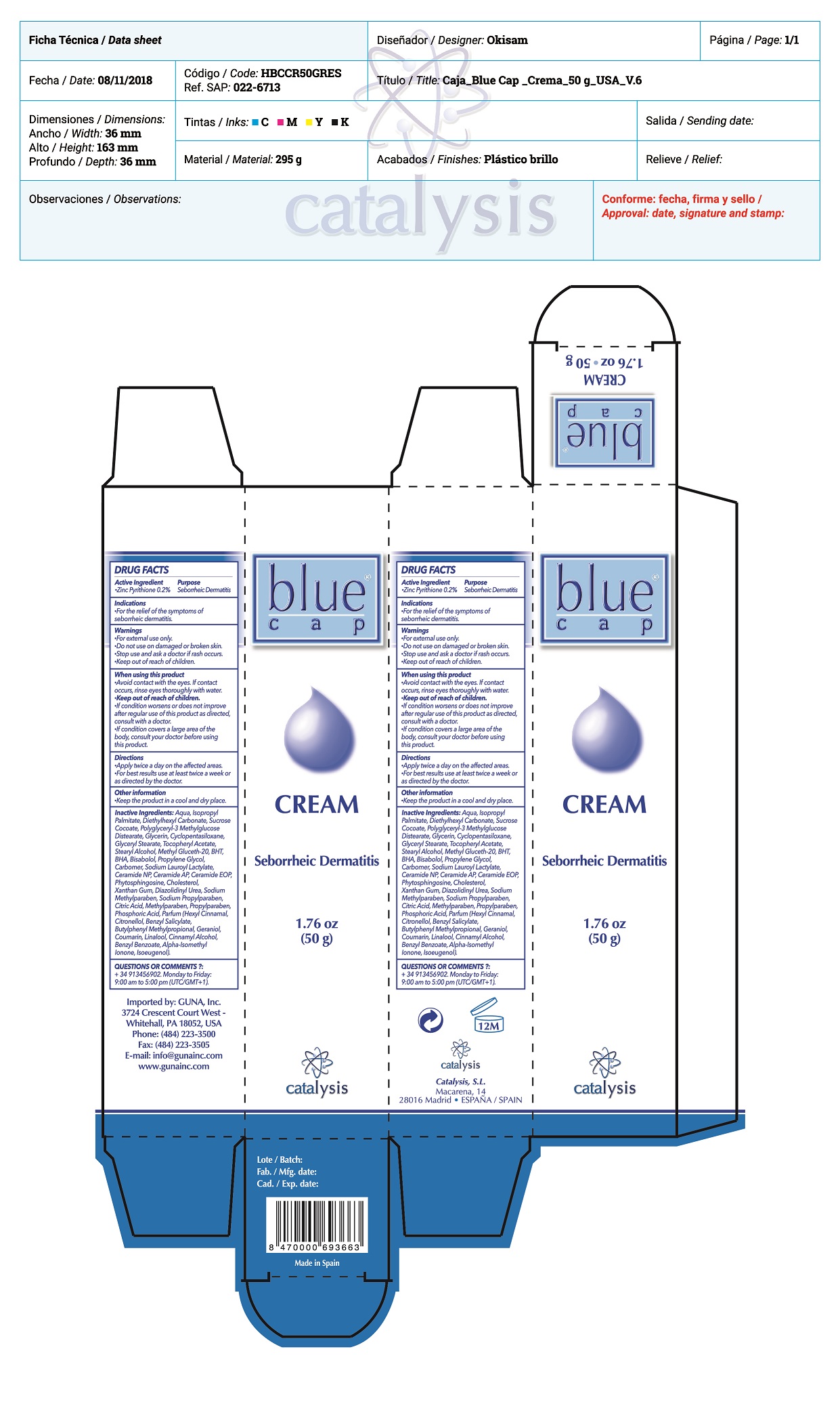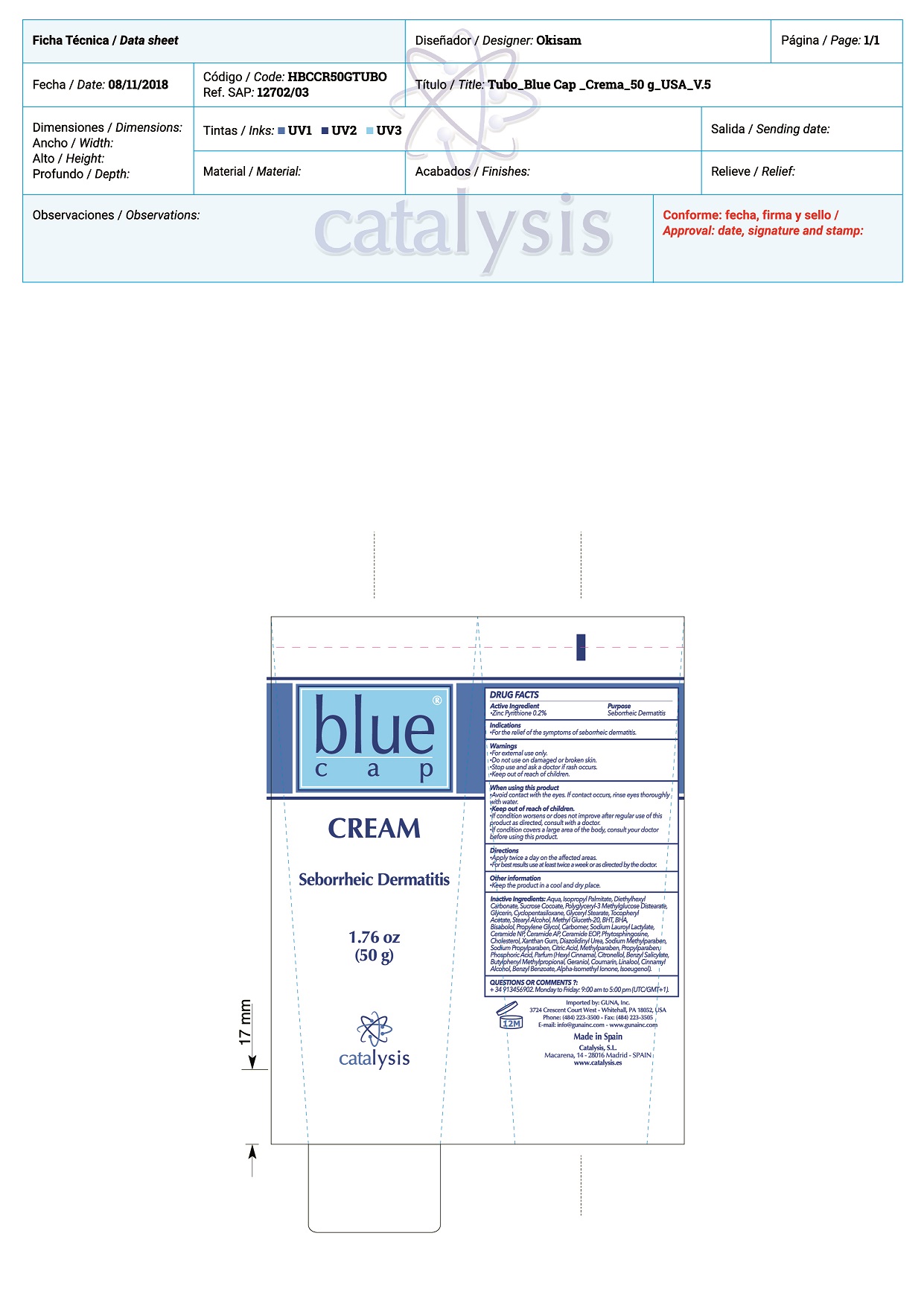 DRUG LABEL: Blue Cap Cream
NDC: 64539-022 | Form: CREAM
Manufacturer: Catalysis, SL
Category: otc | Type: HUMAN OTC DRUG LABEL
Date: 20181125

ACTIVE INGREDIENTS: PYRITHIONE ZINC 0.2 mg/1 g
INACTIVE INGREDIENTS: DIAZOLIDINYL UREA; CERAMIDE AP; WATER; ISOPROPYL PALMITATE; DIETHYLHEXYL CARBONATE; SODIUM LAUROYL LACTYLATE; GLYCERIN; SUCROSE COCOATE; POLYGLYCERYL-3 DISTEARATE; CYCLOMETHICONE 5; GLYCERYL MONOSTEARATE; .ALPHA.-TOCOPHEROL ACETATE; STEARYL ALCOHOL; METHYL GLUCETH-20; LINALOOL, (-)-; BUTYLATED HYDROXYTOLUENE; BUTYLATED HYDROXYANISOLE; PROPANEDIOL; GERANIOL; HYDROXYCITRONELLAL; LEVOMENOL; CITRIC ACID MONOHYDRATE; CARBOXYPOLYMETHYLENE; CERAMIDE NP; CERAMIDE 1; METHYLPARABEN SODIUM; PHYTOSPHINGOSINE; CHOLESTEROL; XANTHAN GUM; PROPYLPARABEN SODIUM; METHYLPARABEN; PROPYLPARABEN; PHOSPHORIC ACID; .BETA.-CITRONELLOL, (S)-; BENZYL SALICYLATE; COUMARIN; BENZYL BENZOATE

Blue Cap Cream

ACTIVE INGREDIENTS PURPOSE

Pyrithione Zinc 0.2%.................. Seborrheic Dermatitis

Warnings

- For external use only.
- Stop use and ask a doctor if rash occurs.
- Do not use on damaged or broken skin
- KEEP out of the reach of children

WARNINGS

- For external use only.
- Stop use and ask a doctor if rash occurs.
- Do not use on damaged or broken skin
- KEEP out of the reach of children

Warnings

Keep out of reach of children

Questions or comments?

+ 34 91 345 6902 M-F 9:00 am to 5:00 pm

Other Information

. keep the product in a cool and dry place

Directions

- apply twice a day on affected area.
- for best results use at least twice a week or as directed by the doctor

DOSAGE AND ADMINISTRATION

- apply twice a day on affected area.
- for best results use at least twice a week or as directed by the doctor

Uses

- For the relief of the symptons of seborrheic dermatitis

Inactive Ingredients

Aqua, Isopropyl Palmitate, Diethylhexyl Carbonate, Sucrose Cocoate, Polyglyceryl-3 Methylglucose Distearate, Glycerin, Cyclopentasiloxane, Glyceryl Stearate. Zinc Pyrithione. Tocopheryl Acetate, Stearyl Alcohol, Methyl Gluceth-20, BHT, BHA, Propylene Glycol, Bisabolol, Carbomer, Sodium Lauroyl Lactylate, Ceramide NP, Ceramide AP, Ceramide EOP, Phytosphingosine, Cholesterol, Xanthan Gum, Diazolidinyl Urea, Sodium Methylparaben, Sodium Propylparaben, Citric Acid, Methylparaben, Propylparaben, Phosphoric Acid, Parfum

Uses

- For the relief of the symptons of seborrheic dermatitis